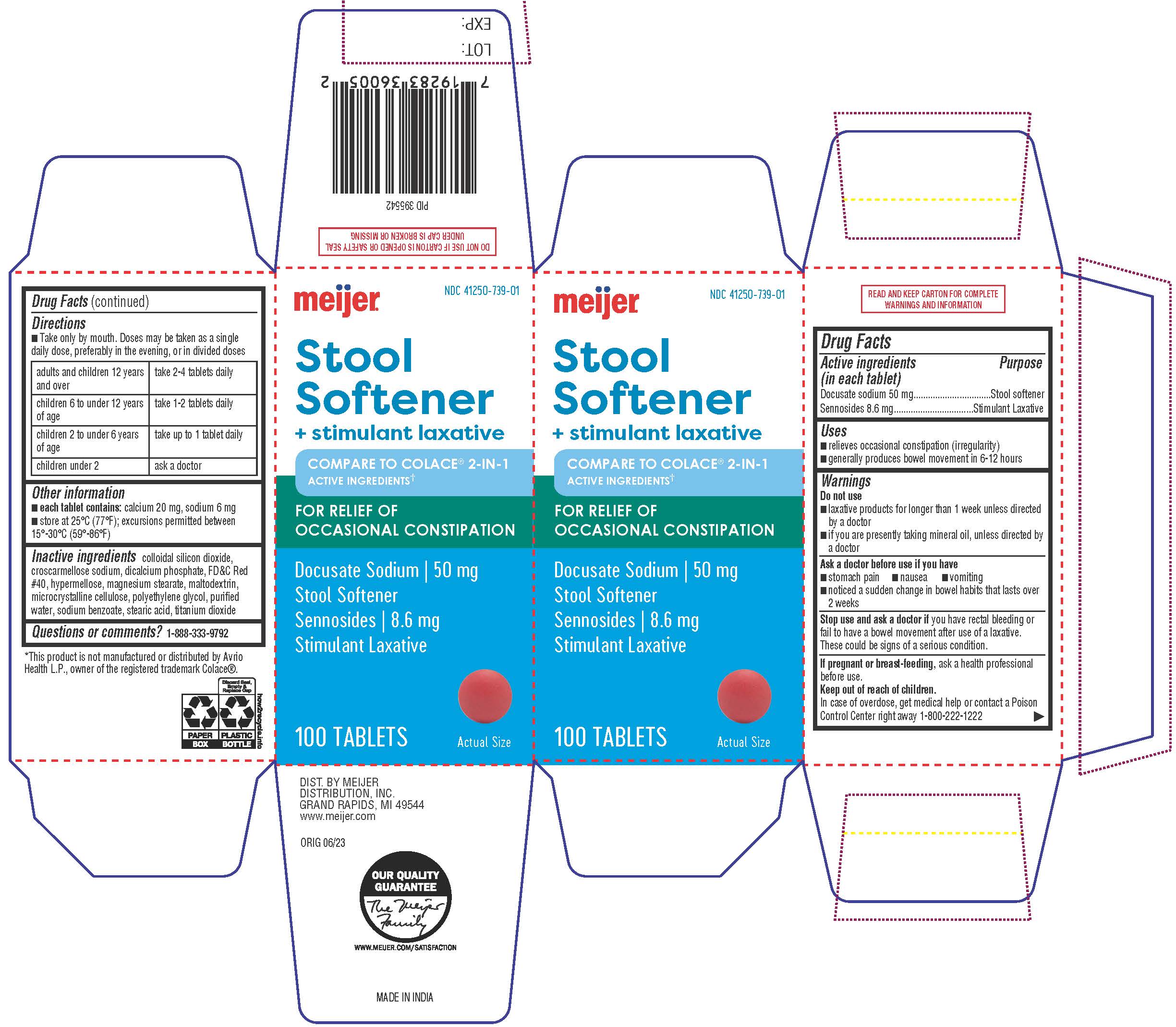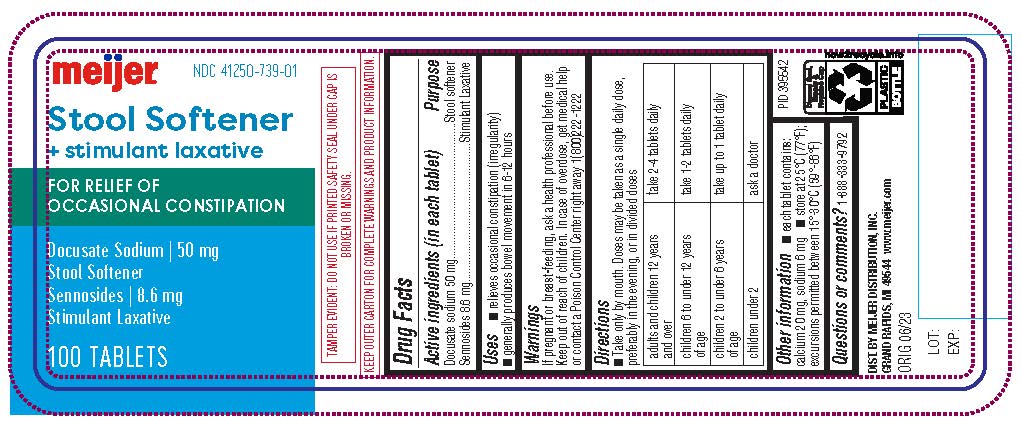 DRUG LABEL: STOOL SOFTENER PLUS STIMULANT LAXATIVE
NDC: 41250-739 | Form: TABLET
Manufacturer: Meijer Distribution Inc.
Category: otc | Type: HUMAN OTC DRUG LABEL
Date: 20241220

ACTIVE INGREDIENTS: DOCUSATE SODIUM 50 mg/1 1; SENNOSIDES 8.6 mg/1 1
INACTIVE INGREDIENTS: SILICON DIOXIDE; CROSCARMELLOSE SODIUM; ANHYDROUS DIBASIC CALCIUM PHOSPHATE; FD&C RED NO. 40; HYPROMELLOSE, UNSPECIFIED; MAGNESIUM STEARATE; MALTODEXTRIN; MICROCRYSTALLINE CELLULOSE; POLYETHYLENE GLYCOL 400; WATER; SODIUM BENZOATE; STEARIC ACID; TITANIUM DIOXIDE

Meijer Stool Softener plus Stimulant Laxative

Active ingredients (in each tablet)

Docusate sodium 50 mg
Sennosides 8.6 mg

Purpose

Stool softener

Stimulant Laxative

Uses

■ relieves occasional constipation (irregularity)
■ generally produces bowel movement in 6-12 hours

Warnings

Do not use

■ laxative products for longer than 1 week unless directed by
a doctor
■ if you are presently taking mineral oil, unless directed by a
doctor

Ask a doctor before use if you have

■ stomach pain ■ nausea ■ vomiting
■ noticed a sudden change in bowel habits that lasts over 2
weeks

Stop use and ask a doctor if

you have rectal bleeding or fail to have a bowel movement after use of a laxative. These could be signs of a serious condition.

PREGNANCY OR BREAST FEEDING

Drug Facts (continued)

If pregnant or breast-feeding,

ask a health professional before use.

Keep out of reach of children.

In case of overdose, get medical help or contact a Poison Control Center right away. 1-800-222-1222

Directions

■ Take only by mouth. Doses may be taken as a single daily
dose, preferably in the evening, or in divided doses

adults and children 12 years and over | take 2-4 tablets daily
children 6 to under 12 years of age | take 1-2 tablets daily
children 2 to under 6 years of age | take up to 1 tablet daily
children under 2 | ask a doctor

Inactive ingredients

Colloidal silicon dioxide, croscarmellose sodium, dicalcium
phosphate, FD&C Red #40, hypermellose, magnesium
stearate, maltodextrin, microcrystalline cellulose, polyethylene
glycol-400, purified water, sodium benzoate, stearic acid,
titanium dioxide

Questions or comments?

1-888-333-9792

DISTRIBUTED BY:

MEIJER DISTRIBUTION, INC.

GRAND RAPIDS, MI 49544

PRINCIPAL DISPLAY PANEL

COMPARE TO THE ACTIVE
INGREDIENTS OF PERI-COLACE®†

Stool Softener

with Stimulant Laxative

Docusate Sodium 50 mg
Sennosides 8.6 mg

Relieves
Constipation

ACTUAL SIZE

100 TABLETS